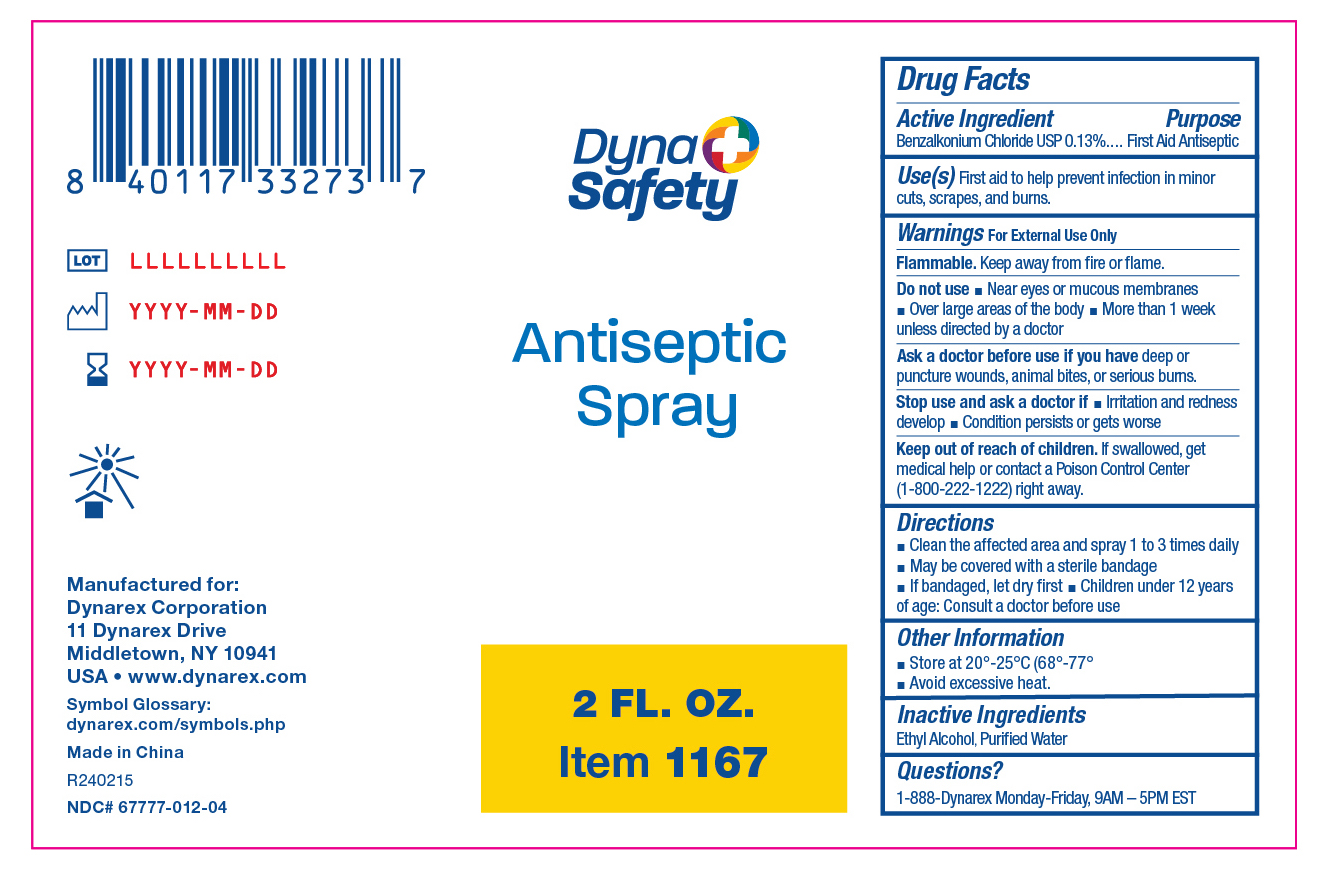 DRUG LABEL: Antiseptic
NDC: 67777-012 | Form: SPRAY
Manufacturer: Dynarex Corporation
Category: otc | Type: HUMAN OTC DRUG LABEL
Date: 20240216

ACTIVE INGREDIENTS: BENZALKONIUM CHLORIDE 0.13 mg/1 mL
INACTIVE INGREDIENTS: WATER; ALCOHOL 95%

1167 Antiseptic Spray

Active Ingredient

Benzalkonium Chloride 0.13%

Purpose

First Aid Antiseptic

Use(s)

First aid to help prevent infection in minor cuts, scrapes, and burns

Warnings

For External Use Only

Flammable. Keep away from fire or flame.

Do not use

• Near eyes or mucous membranes • Over large areas of the body • More than 1 week unless directed by a doctor

Ask a doctor before use if you have

Deep or puncture wounds, animal bites, or serious burns.

Stop use and ask a doctor if

• Irritation and redness develop • Condition persists or gets worse

Keep out of reach of children

If swallowed, get medical help or contact a Poison Control Center (1-800-222-1222) right away.

Directions

• Clean the affected area and spray 1 to 3 times daily

• May be covered with a sterile bandage

• If bandaged, let dry first

• Children under 12 years of age: Consult a doctor before use

Other Information

• Store at 20º-25ºC (68°-77ºF)

• Avoid excessive heat

Inactive Ingredients

Ethyl Alcohol, Purified Water

Questions?

1-888-Dynarex Monday - Friday, 9AM - 5PM EST

Label

1167 Label